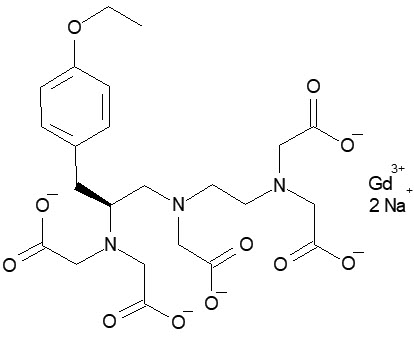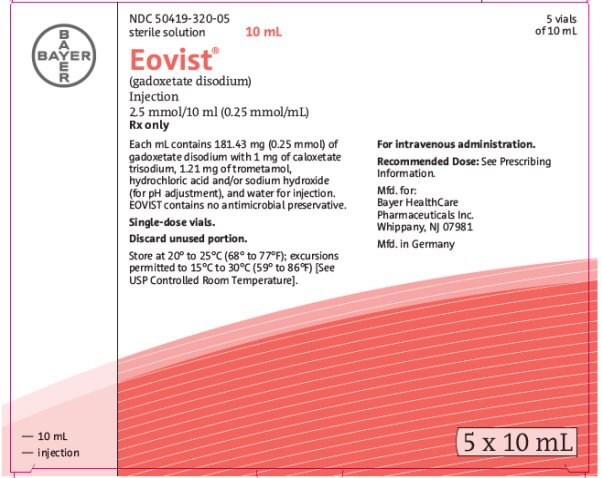 DRUG LABEL: EOVIST
NDC: 50419-320 | Form: INJECTION, SOLUTION
Manufacturer: Bayer HealthCare Pharmaceuticals Inc.
Category: prescription | Type: HUMAN PRESCRIPTION DRUG LABEL
Date: 20260227

ACTIVE INGREDIENTS: GADOXETATE DISODIUM 181.43 mg/1 mL
INACTIVE INGREDIENTS: TROMETHAMINE; HYDROCHLORIC ACID; SODIUM HYDROXIDE; WATER

HIGHLIGHTS OF PRESCRIBING INFORMATION

These highlights do not include all the information needed to use EOVIST® safely and effectively. See full prescribing information for EOVIST.
EOVIST (gadoxetate disodium) injection, for intravenous use
Initial U.S. Approval: 2008

WARNING: RISK ASSOCIATED WITH INTRATHECAL USE and NEPHROGENIC SYSTEMIC FIBROSIS

See full prescribing information for complete boxed warning.

- Intrathecal administration of gadolinium-based contrast agents (GBCAs) can cause serious adverse reactions including death, coma, encephalopathy, and seizures. EOVIST is not approved for intrathecal use. (5.1)
- GBCAs increase the risk for nephrogenic systemic fibrosis (NSF) among patients with impaired elimination of the drugs. Avoid use of EOVIST in these patients unless the diagnostic information is essential and not available with non-contrasted MRI or other modalities.
  The risk for NSF appears highest among patients with:
  - Chronic, severe kidney disease (GFR < 30 mL/min/1.73m^2), or
  - Acute kidney injury.
  Screen patients for acute kidney injury and other conditions that may reduce renal function.
  For patients at risk for chronically reduced renal function (for example, age >60 years, hypertension or diabetes), estimate the glomerular filtration rate (GFR) through laboratory testing. (5.2)

1 INDICATIONS AND USAGE

EOVIST is a gadolinium-based contrast agent indicated for use in magnetic resonance imaging (MRI) of the liver to detect and characterize lesions in adult and pediatric patients, including term neonates, with known or suspected focal liver disease. (1)

2 DOSAGE AND ADMINISTRATION

- Recommended dose is 0.025 mmol/kg actual body weight (equivalent to 0.1 mL/kg) administered by intravenous injection at 1 mL/sec to 2 mL/sec. (2.1)
- See Full Prescribing Information for administration and imaging instructions. (2.2, 2.3)

3 DOSAGE FORMS AND STRENGTHS

Injection: 0.025 mmol/mL of gadoxetate disodium

- 2.5 mmol/10 mL (0.25 mmol/mL) in single-dose vial
- 3.75 mmol/15 mL (0.25 mmol/mL) in single-dose vial (3)

4 CONTRAINDICATIONS

History of severe hypersensitivity reaction to EOVIST (4)

5 WARNINGS AND PRECAUTIONS

- Hypersensitivity Reactions: Anaphylactic and other hypersensitivity reactions with cardiovascular, respiratory and cutaneous manifestations, ranging from mild to severe reactions including shock can occur. Monitor patients closely for need of emergency cardiorespiratory support (5.3)
- Gadolinium Retention: Gadolinium is retained for months or years in brain, bone, and other organs. (5.4)

6 ADVERSE REACTIONS

Most common adverse reactions (incidence ≥ 0.5%) are nausea, headache, feeling hot, dizziness, and back pain. (6.1)

To report SUSPECTED ADVERSE REACTIONS, contact Bayer HealthCare Pharmaceuticals Inc. at 1-888-84-BAYER (1-888-842-2937) or FDA at 1-800-FDA-1088 or www.fda.gov/medwatch.

7 DRUG INTERACTIONS

Serum iron determination using complexometric methods (for example, ferrocene complexation method) may result in falsely high or low values for up to 24 hours. Conduct serum iron tests either before or at least 24 hours following administration. (7)

8 USE IN SPECIFIC POPULATIONS

Pregnancy: Use only if imaging is essential during pregnancy and cannot be delayed. (8.1)

FULL PRESCRIBING INFORMATION

WARNING: RISK ASSOCIATED WITH INTRATHECAL USE and NEPHROGENIC SYSTEMIC FIBROSIS

Risk Associated with Intrathecal Use

Intrathecal administration of gadolinium-based contrast agents (GBCAs) can cause serious adverse reactions including death, coma, encephalopathy, and seizures. EOVIST is not approved for intrathecal use [see Warnings and Precautions (5.1)].

Nephrogenic Systemic Fibrosis

GBCAs increase the risk for nephrogenic systemic fibrosis (NSF) among patients with impaired elimination of the drugs. Avoid use of EOVIST in these patients unless the diagnostic information is essential and not available with non-contrasted MRI or other modalities. NSF may result in fatal or debilitating fibrosis affecting the skin, muscle and internal organs.

The risk for NSF appears highest among patients with:

- Chronic, severe kidney disease (GFR < 30 mL/min/1.73m^2), or
- Acute kidney injury.

Screen patients for acute kidney injury and other conditions that may reduce renal function. For patients at risk for chronically reduced renal function (for example, age > 60 years, hypertension or diabetes), estimate the glomerular filtration rate (GFR) through laboratory testing.

For patients at highest risk for NSF, do not exceed the recommended EOVIST dose and allow a sufficient period of time for elimination of the drug from the body prior to any re-administration [see Warnings and Precautions (5.2)].

1 INDICATIONS AND USAGE

EOVIST is indicated for use in magnetic resonance imaging (MRI) of the liver to detect and characterize lesions in adult and pediatric patients, including term neonates, with known or suspected focal liver disease.

2 DOSAGE AND ADMINISTRATION

2.1 Recommended Dose

The recommended dose of EOVIST for adult and pediatric patients, including term neonates, is 0.025 mmol/kg actual body weight (equivalent to 0.1 mL/kg) administered intravenously at a recommended rate of 1 mL/sec to 2 mL/sec.

2.2 Administration and Drug Handling

- EOVIST is for intravenous use only and must not be administered intrathecally [see Warnings and Precautions (5.1)].
- Use aseptic technique when preparing and administering EOVIST.
- Visually inspect EOVIST for particulate matter and discoloration prior to administration. Do not use the solution if it is discolored or if particulate matter is present.
- Use EOVIST immediately after obtaining appropriate dose from vial.
- Pierce the rubber stopper only once. Discard any unused portion of an EOVIST vial.
- Do not mix EOVIST with other medications and do not administer EOVIST in the same intravenous line simultaneously with other medications.
- Flush the intravenous cannula with 0.9% Sodium Chloride Injection after EOVIST injection.

2.3 Imaging

- Liver lesions are detected and characterized with pre-contrast MRI and EOVIST MRI obtained during dynamic and hepatocyte imaging phases. Perform a pre-contrast MRI, inject EOVIST, and begin dynamic imaging approximately 15 seconds to 25 seconds after completion of the injection. Dynamic imaging consists of the arterial, the porto-venous (approximately 60 seconds post-injection), and the blood equilibrium (approximately 120 seconds) phases.
- Begin the hepatocyte imaging phase approximately 20 minutes post-injection. Hepatocyte phase imaging may be performed up to 120 minutes post-injection.
- Elevated intrinsic levels of bilirubin (>3 mg/dL) or ferritin can reduce the hepatic contrast effect of EOVIST. Perform MR imaging no later than 60 minutes following EOVIST administration to patients with these laboratory abnormalities, including patients who have elevated ferritin levels due to hemodialysis [see Warnings and Precautions (5.8) and Use in Specific Populations (8.6, 8.7)].
- Lesions with no or minimal hepatocyte function (cysts, metastases, and the majority of hepatocellular carcinomas) generally will not accumulate EOVIST. Well-differentiated hepatocellular carcinoma may contain functioning hepatocytes and can show some enhancement in the hepatocyte imaging phase. Additional clinical information is therefore needed to support a diagnosis of hepatocellular carcinoma.

3 DOSAGE FORMS AND STRENGTHS

Injection: 0.25 mmol/mL of gadoxetate disodium as a clear and colorless to pale yellow solution available in the following strengths:

- 2.5 mmol/10 mL (0.25 mmol/mL) in single-dose vial
- 3.75 mmol/15 mL (0.25 mmol/mL) in single-dose vial

4 CONTRAINDICATIONS

EOVIST is contraindicated in patients with history of severe hypersensitivity reactions to EOVIST [see Warnings and Precautions (5.3)].

5 WARNINGS AND PRECAUTIONS

5.1 Risk Associated with Intrathecal Use

Intrathecal administration of GBCAs can cause serious adverse reactions including death, coma, encephalopathy, and seizures. The safety and effectiveness of EOVIST have not been established with intrathecal use. EOVIST is not approved for intrathecal use [see Dosage and Administration (2.2)].

5.2 Nephrogenic Systemic Fibrosis

GBCAs increase the risk for nephrogenic systemic fibrosis (NSF) among patients with impaired elimination of the drugs. Avoid use of EOVIST among these patients unless the diagnostic information is essential and not available with non-contrast enhanced MRI or other modalities. The GBCA-associated NSF risk appears highest for patients with chronic, severe kidney disease (GFR < 30 mL/min/1.73m^2) as well as patients with acute kidney injury. The risk appears lower for patients with chronic, moderate kidney disease (GFR 30 to 59 mL/min/1.73m^2) and little, if any, for patients with chronic, mild kidney disease (GFR 60 to 89 mL/min/1.73m^2). NSF may result in fatal or debilitating fibrosis affecting the skin, muscle and internal organs. Report any diagnosis of NSF following EOVIST administration to Bayer HealthCare (1-888-842-2937) or FDA at 1-800-FDA-1088 or www.fda.gov/medwatch.

Screen patients for acute kidney injury and other conditions that may reduce renal function. Features of acute kidney injury consist of rapid (over hours to days) and usually reversible decrease in kidney function, commonly in the setting of surgery, severe infection, injury or drug-induced kidney toxicity. Serum creatinine levels and estimated GFR may not reliably assess renal function in the setting of acute kidney injury. For patients at risk for chronically reduced renal function (for example, age > 60 years, diabetes mellitus or chronic hypertension), estimate the GFR through laboratory testing.

Among the factors that may increase the risk for NSF are repeated or higher than recommended doses of a GBCA and degree of renal impairment at the time of exposure. Record the specific GBCA and the dose administrated to a patient. For patients at highest risk for NSF, do not exceed the recommended EOVIST dose and allow a sufficient period of time for elimination of the drug prior to any re-administration. For patients receiving hemodialysis, consider the prompt initiation of hemodialysis following the administration of a GBCA in order to enhance the contrast agent's elimination [see Use in Specific Populations (8.6) and Clinical Pharmacology (12.3)]. The usefulness of hemodialysis in the prevention of NSF is unknown.

5.3 Hypersensitivity Reactions

Anaphylactic and other hypersensitivity reactions with cardiovascular, respiratory and cutaneous manifestations, ranging from mild to severe, including shock have occurred following EOVIST administration. Most hypersensitivity reactions to EOVIST have occurred within half an hour after administration. Delayed reactions can occur up to several days after EOVIST administration [see Adverse Reactions (6.2)].

- Before EOVIST administration, assess all patients for any history of a reaction to contrast media, bronchial asthma and allergic disorders. These patients may have an increased risk for a hypersensitivity reaction to EOVIST.
- EOVIST is contraindicated in patients with history of hypersensitivity reactions to EOVIST [see Contraindications (4)].
- Administer EOVIST only in situations where trained personnel and therapies are promptly available for the treatment of hypersensitivity reactions, including personnel trained in resuscitation.
- Observe patients for signs and symptoms of hypersensitivity reactions during and following EOVIST administration.

5.4 Gadolinium Retention

Gadolinium is retained for months or years in several organs. The highest concentrations (nanomoles per gram of tissue) have been identified in the bone, followed by other organs (for example, brain, skin, kidney, liver, and spleen). The duration of retention also varies by tissue and is longest in bone. Linear GBCAs cause more retention than macrocyclic GBCAs. At equivalent doses, gadolinium retention varies among the linear agents with gadodiamide causing greater retention than other linear agents such as gadoxetate disodium and gadobenate dimeglumine. Retention is lowest and similar among the macrocyclic GBCAs such as gadoterate meglumine, gadobutrol, gadoteridol, and gadopiclenol.

Consequences of gadolinium retention in the brain have not been established. Pathologic and clinical consequences of GBCA administration and retention in skin and other organs have been established in patients with impaired renal function [see Warnings and Precautions (5.2)]. There are rare reports of pathologic skin changes in patients with normal renal function. Adverse events involving multiple organ systems have been reported in patients with normal renal function without an established causal link to gadolinium retention [see Adverse Reactions (6.2)].

While clinical consequences of gadolinium retention have not been established in patients with normal renal function, certain patients might be at higher risk. These include patients requiring multiple lifetime doses, pregnant and pediatric patients, and patients with inflammatory conditions. Consider the retention characteristics of the agent when choosing a GBCA for these patients. Minimize repetitive GBCA imaging studies particularly closely spaced studies, when possible.

5.5 Acute Kidney Injury

In patients with chronic renal impairment, acute kidney injury sometimes requiring dialysis has been observed with the use of some GBCAs. The risk of acute kidney injury might be lower with EOVIST due to its dual excretory pathways. Do not exceed the recommended dose; the risk of acute kidney injury may increase with higher than recommended doses.

5.6 Extravasation and Injection Site Reactions

Injection site reactions such as pain have been reported in clinical studies with EOVIST [see Adverse Reactions (6.1)]. Extravasation into tissues during EOVIST administration may result in local tissue reactions such as myocyte necrosis and inflammation [see Nonclinical Toxicology (13.2)]. Ensure catheter and venous patency before the injection of EOVIST.

5.7 Interference with Laboratory Tests

EOVIST can interfere with serum iron determination using complexometric methods (for example, ferrocene complexation method) [see Drug Interactions (7)].

5.8 Interference with Visualization of Liver Lesions

Severe renal or hepatic failure may impair EOVIST imaging performance. In patients with end-stage renal failure, hepatic contrast was markedly reduced and was attributed to elevated serum ferritin levels. In patients with abnormally high (>3 mg/dL) serum bilirubin, reduced hepatic contrast was observed. If EOVIST is used in these patients, complete MRI no later than 60 minutes after EOVIST administration and use a paired non-contrast and contrast MRI set for diagnosis [see Dosage and Administration (2.3)].

6 ADVERSE REACTIONS

The following clinically significant adverse reactions are discussed elsewhere in the labeling:

- Nephrogenic systemic fibrosis [see Warnings and Precautions (5.2)]
- Hypersensitivity reactions [see Contraindications (4) and Warnings and Precautions (5.3)]

6.1 Clinical Trials Experience

Because clinical trials are conducted under widely varying conditions, adverse reaction rates observed in the clinical trials of a drug cannot be directly compared to rates in the clinical trials of another drug and may not reflect the rates observed in clinical practice.

Adverse Reactions in Adults

The safety of EOVIST was evaluated in 1,989 adult subjects who received EOVIST in clinical trials. Overall, 59% of the subjects were male, and the racial and ethnic distribution was 64% White, 22% Asian, 3% Hispanic or Latino, 2% Black or African American, and 0.5% other ethnic groups. The average age was 57 years (age range from 19 to 84 years).

Table 1 lists adverse reactions that occurred in ≥ 0.1% of subjects who received the recommended dose of EOVIST in clinical trials.

Table 1: Adverse Reactions Reported in ≥ 0.1% of Adult Subjects who Received EOVIST in Clinical Trials
Adverse Reaction | EOVIST n = 1,581 Rate (%)
Nausea | 1.1
Headache | 1.1
Feeling hot | 0.8
Dizziness | 0.6
Back pain | 0.6
Vomiting | 0.4
Blood pressure increased | 0.4
Injection site reactions (pain, burning, coldness, extravasation, irritation) | 0.4
Dysgeusia | 0.4
Paresthesia | 0.3
Flushing | 0.3
Parosmia | 0.3
Pruritus (generalized, eye) | 0.3
Rash | 0.3
Respiratory disorders (dyspnea, respiratory distress) | 0.2
Fatigue | 0.2
Chest pain | 0.1
Vertigo | 0.1
Dry mouth | 0.1
Chills | 0.1
Feeling abnormal | 0.1

Adverse reactions that occurred with a frequency of < 0.1% in subjects who received EOVIST include: tremor, akathisia, bundle branch block, palpitation, oral discomfort, salivary hypersecretion, maculopapular rash, hyperhidrosis, discomfort, and malaise.

Elevation of serum iron values and serum bilirubin laboratory values were reported in < 1% of subjects after administration of EOVIST. The values did not exceed more than 3 times the baseline values and returned to baseline within 1 to 4 days.

Adverse Reactions in Pediatric Patients

In a study of EOVIST in 52 pediatric patients between 2 months of age and 18 years of age, no new safety signals were observed [see Use in Specific Populations (8.4)].

6.2 Postmarketing Experience

The following additional adverse reactions have been identified during the postmarketing use of EOVIST or other GBCAs. Because these reactions are reported voluntarily from a population of uncertain size, it is not possible to reliably estimate their frequency or establish a causal relationship to drug exposure.

Cardiac Disorders: Tachycardia

Gastrointestinal Disorders: Acute pancreatitis with onset within 48 hours after GBCA administration

General Disorders and Administration Site Conditions: Fatigue, asthenia, pain syndromes, and heterogeneous clusters of symptoms in the neurological, cutaneous, and musculoskeletal systems with variable onset and duration after GBCA administration [see Warnings and Precautions (5.4)]

Immune System Disorders: Hypersensitivity reactions (anaphylactic shock, hypotension, pharyngolaryngeal edema, urticaria, face edema, rhinitis, conjunctivitis, abdominal pain, hypoesthesia, sneezing, cough and pallor)

Psychiatric Disorders: Restlessness

Renal Disorders: Nephrogenic systemic fibrosis

Respiratory, Thoracic, and Mediastinal Disorders: Acute respiratory distress syndrome, pulmonary edema

Skin Disorders: Gadolinium associated plaques

7 DRUG INTERACTIONS

Serum Iron Test

EOVIST contains caloxetate trisodium that can interfere with serum iron determination using complexometric methods (for example, ferrocene complexation method) and may result in falsely high or low values for up to 24 hours after the administration of EOVIST. Conduct serum iron tests either before or at least 24 hours following administration of EOVIST.

8 USE IN SPECIFIC POPULATIONS

8.1 Pregnancy

Risk Summary

GBCAs cross the placenta and result in fetal exposure. In human placental imaging studies, contrast was visualized in the placenta and fetal tissues after maternal GBCA administration. Based on animal studies, use of GBCAs during pregnancy may result in fetal gadolinium retention.

Published epidemiological studies on the association between GBCAs and adverse fetal outcomes have reported inconsistent findings and have important methodological limitations (see Data).

In animal reproduction studies, no teratogenicity was observed with repeated daily intravenous administration of gadoxetate disodium to rats during organogenesis at doses up to 32 times the recommended single human dose; however, an increase in preimplantation loss was noted at doses 3.2 times the single human dose. Post implantation loss was observed with repeated daily intravenous administration of gadoxetate disodium to rabbits on gestation days 6 through 18 at doses 26 times the recommended single human dose (see Data). Because of the potential risks of gadolinium to the fetus, use EOVIST only if imaging is essential during pregnancy and cannot be delayed.

The background risk of major birth defects and miscarriage for the indicated population is unknown. All pregnancies have a background risk of birth defect, loss, or other adverse outcomes. In the U.S. general population, the estimated background risk of major birth defects and miscarriage in clinically recognized pregnancies is 2% to 4% and 15% to 20%, respectively.

Data

Human Data

Available data regarding exposure to GBCAs during pregnancy from published epidemiological studies are not sufficient to assess the risk of adverse fetal and neonatal effects that may be associated with GBCAs. A retrospective cohort study of over 1.4 million pregnancies in Ontario, Canada, comparing pregnant women who had a GBCA MRI to pregnant women who did not have an MRI, reported a higher occurrence of stillbirths and neonatal deaths in the group receiving GBCA MRI. Limitations of this study include a lack of comparison with non-contrast MRI and lack of information about the maternal indication for MRI. Another retrospective cohort study of over 11 million pregnancies in the Medicaid database found no increased risk of fetal or neonatal death or Neonatal Intensive Care Unit admission when comparing pregnancies exposed to GBCA MRI versus non-contrast MRI. These two retrospective studies assessed a limited number of potential pregnancy outcomes and did not evaluate the full spectrum of potential fetal risk.

Animal Data

Gadolinium Retention

GBCAs administered to pregnant non-human primates (0.1 mmol/kg on gestational days 85 and 135) result in measurable gadolinium concentration in the offspring in bone, brain, skin, liver, kidney, and spleen for at least 7 months. GBCAs administered to pregnant mice (2 mmol/kg daily on gestational days 16 through 19) result in measurable gadolinium concentrations in the pups in bone, brain, kidney, liver, blood, muscle, and spleen at one month postnatal age.

Reproductive Toxicology

Animal reproductive and developmental toxicity studies were done in rats and rabbits. Gadoxetate disodium was not teratogenic when given intravenously during organogenesis to pregnant rats at doses up to 32 times the recommended single human dose (mmol/m^2 basis). However, an increase in preimplantation loss was noted at 3.2 times the human dose (mmol/m^2 basis). Compared to untreated controls, rates of post implantation loss and absorption increased and litter size decreased when pregnant rabbits received gadoxetate disodium at doses 26 times the recommended human single dose (mmol/m^2 basis). This occurred without evidence of maternal toxicity. Because pregnant animals received repeated daily doses of gadoxetate disodium, their overall exposure was significantly higher than that achieved with the standard single dose administered to humans.

8.2 Lactation

Risk Summary

There is no information regarding the presence of gadoxetate disodium in human milk, the effects of the drug in a breastfed infant, or the effects of the drug on milk production. However, published lactation data on other GBCAs report that 0.01 to 0.04% of the maternal gadolinium dose is present in breast milk and there is limited GBCA gastrointestinal absorption in the breastfed infant. In rat lactation studies with [^153Gd] gadoxetate disodium, less than 0.5% of the total administered radioactivity was transferred to the nursing pup (see Data).

Clinical Considerations

A lactating woman may consider interrupting breastfeeding and pumping and discarding breast milk for up to 10 hours after EOVIST administration in order to minimize exposure to a breastfed infant.

Data

In lactating rats given 0.1 mmol/kg [^153Gd] gadoxetate disodium, less than 0.5% of the total administered radioactivity was transferred to the neonates via maternal milk, mostly within 2 hours.

8.4 Pediatric Use

The safety and effectiveness of EOVIST for magnetic resonance imaging (MRI) of the liver to detect and characterize lesions have been established in pediatric patients, including term neonates. Use of EOVIST in this age group is supported by evidence from adequate and well-controlled studies in adults and an observational study in 52 pediatric patients between 2 months of age and 18 years of age who were referred for evaluation of suspected or known focal liver lesions. In this observational study, EOVIST improved border delineation and increased contrast of the primary lesion in the majority of patients when compared to non-contrast images [see Adverse Reactions (6.1) and Clinical Studies (14)].

The safety and effectiveness of EOVIST have not been established in preterm neonates.

8.5 Geriatric Use

In clinical studies of EOVIST, 674 (34%) patients were 65 years of age and over, while 20 (1%) were 80 years of age and over. No overall differences in safety or effectiveness were observed between these subjects and younger subjects, and other reported clinical experience has not identified differences between the elderly and younger patients.

In general, use of EOVIST in an elderly patient should be cautious, reflecting the greater frequency of decreased hepatic, renal or cardiac function and of concomitant disease or other drug therapy.

8.6 Renal Impairment

In patients with renal impairment, the exposure of gadoxetate is increased compared to patients with normal renal function. This may increase the risk of adverse reactions such as nephrogenic systemic fibrosis (NSF). EOVIST can be removed by hemodialysis [see Warnings and Precautions (5.2) and Clinical Pharmacology (12.3)].

In patients with end-stage renal failure, hepatic contrast was reduced, which was attributed to significantly elevated serum ferritin levels [see Dosage and Administration (2.3) and Warnings and Precautions (5.8)].

In patients with moderate renal impairment, hepatic contrast did not differ among the groups.

8.7 Hepatic Impairment

In patients with severe hepatic impairment, the exposure of gadoxetate is increased and EOVIST imaging performance may be impaired [see Dosage and Administration (2.3), Warnings and Precautions (5.8), and Clinical Pharmacology (12.3)].

In patients with mild or moderate hepatic impairment, the exposure of gadoxetate was moderately increased compared to healthy subjects with normal liver function, but hepatic contrast signal did not differ among the groups.

A dose adjustment is not necessary for patients with hepatic impairment.

In clinical studies, 489 patients had a diagnosis of liver cirrhosis (Child-Pugh category A, n = 270; category B, n = 98; category C, n = 24; unknown category, n = 97). No difference in diagnostic performance and safety was observed among these patients.

10 OVERDOSAGE

In case of inadvertent overdosage in patients with severely impaired renal and/or hepatic function, EOVIST can be partially removed by hemodialysis [see Clinical Pharmacology (12.3)].

For additional overdose management recommendations, consider contacting the Poison Help line at 1-800-222-1222 or consulting a medical toxicologist.

11 DESCRIPTION

EOVIST (gadoxetate disodium) injection is a paramagnetic gadolinium-based contrast agent for intravenous use.

Gadoxetate disodium (Gd-EOB-DTPA) is a highly water-soluble, hydrophilic compound with a lipophilic moiety, the ethoxybenzyl group (EOB). EOB-DTPA forms a stable complex with the paramagnetic gadolinium ion with a thermodynamic stability of log KGdL=-23.46. The chemical name for gadoxetate disodium is (4S)-4-(4-Ethoxybenzyl)-3,6,9-tris(carboxylatomethyl)-3,6,9-triazaundecanedioic acid, gadolinium complex, disodium salt. Gadoxetate disodium has a molecular weight of 725.72 and an empirical formula of GdC23H28N3O11Na2. The structural formula of gadoxetate disodium is:

EOVIST is a sterile, clear, colorless to pale yellow solution. Each mL contains 181.43 mg (0.25 mmol) of gadoxetate disodium (containing 0.25 mmol of gadolinium) and the following inactive ingredients: 1 mg of caloxetate trisodium, 1.21 mg of trometamol, hydrochloric acid and/or sodium hydroxide (for pH adjustment), and water for injection. EOVIST contains no antimicrobial preservative.

Pertinent physiochemical properties of EOVIST are provided in Table 2.

Table 2: Physicochemical Properties of EOVIST
Parameter | Value
Osmolality at 37°C (Osm/kg H2O) | 0.688
Viscosity at 37°C (cP) | 1.19
Density at 37°C (g/mL) | 1.088
pH | 6.8-8

12 CLINICAL PHARMACOLOGY

12.1 Mechanism of Action

Gadoxetate is a paramagnetic molecule that develops a magnetic moment when placed in a magnetic field. The magnetic moment alters the relaxation rates of water protons in its vicinity in the body, leading to an increase in signal intensity (brightness) of tissues. Gadoxetate is selectively taken up by hepatocytes, resulting in increased signal intensity in liver tissue.

12.2 Pharmacodynamics

In MRI, visualization of normal and pathological tissue depends in part on variations in the radiofrequency signal intensity that occurs with:

- Differences in proton density
- Differences of the spin-lattice or longitudinal relaxation times (T1)
- Differences in the spin-spin or transverse relaxation time (T2)

When placed in a magnetic field, gadoxetate shortens the T1 and T2 relaxation times in targeted tissues. The extent to which a contrast agent can affect the relaxation rate of tissue water (1/T1 or 1/T2) is termed relaxivity (r1 or r2). The relaxivity of gadoxetate in human plasma is about 6.9 L/mmol/sec at pH 7, 37°C and 1.5 T.

12.3 Pharmacokinetics

Distribution

Gadoxetate exhibits a biphasic mode of action: first, distribution in the extracellular space after injection and subsequently, selective uptake by hepatocytes (and biliary excretion) due to the lipophilic (EOB) moiety. After intravenous administration, the plasma concentration time profile of gadoxetate is characterized by a bi-exponential decline. The total distribution volume of gadoxetate at steady state is about 0.21 L/kg (extracellular space); plasma protein binding is less than 10%. Following GBCA administration, gadolinium is present for months or years in brain, bone, skin, and other organs [see Warnings and Precautions (5.4)].

Elimination

The mean terminal elimination half-life of gadoxetate (0.01 to 0.1 mmol/kg) has been observed in healthy subjects of 22 to 39 years of age to be 0.91 to 0.95 hour. The pharmacokinetics are dose-linear up to a dose of 0.1 mmol/kg (4 times the recommended dose).

A total serum clearance (Cltot) was 250 mL/min, whereas the renal clearance (Clr) corresponds to about 120 mL/min, a value similar to the glomerular filtration rate in healthy subjects.

Metabolism

Gadoxetate is not metabolized.

Excretion

Gadoxetate is equally eliminated via the renal and hepatobiliary routes.

Specific Populations

Geriatric Patients

In a clinical pharmacology study, the AUC and terminal half-life of gadoxetate were slightly increased (1.2-fold and 1.3-fold, respectively) and total clearance was decreased by 0.8-fold in geriatric patients compared to non-geriatric patients.

Patients with Renal Impairment

In a study of patients with end-stage renal failure, the AUC was increased about 6-fold and the terminal half-life was prolonged about 12-fold. Approximately 30% of the injected dose was removed by dialysis in a single 3-hour dialysis session, which started 1 hour after an EOVIST dose. Gadoxetate was almost completely eliminated via hemodialysis and biliary excretion within the observation period of 6 days, predominantly within the first 3 days [see Use in Specific Populations (8.6)].

In patients with moderate renal impairment, a moderate increase in AUC and terminal half-life (1.5-fold and 1.2-fold, respectively) was observed in comparison to healthy subjects with normal renal function.

Patients with Hepatic Impairment

In patients with severe hepatic impairment, especially in patients with abnormally high (> 3 mg/dL) serum bilirubin levels, the AUC of gadoxetate was increased up to 60% and the elimination half-life was increased up to 49%. The hepatobiliary excretion substantially decreased to about 5% of the administered dose [see Use in Specific Populations (8.7)].

In patients with mild or moderate hepatic impairment, a slight to moderate increase in plasma AUC (1.6-fold), half-life (1.1-fold), and urinary excretion (1.3-fold), as well as decrease in hepatobiliary excretion (0.7-fold) was observed in comparison to healthy subjects with normal liver function.

13 NONCLINICAL TOXICOLOGY

13.1 Carcinogenesis, Mutagenesis, Impairment of Fertility

Carcinogenesis

No carcinogenicity studies of EOVIST have been conducted.

Mutagenesis

Gadoxetate disodium was not mutagenic in in vitro reverse mutation tests in bacteria, or in chromosome aberration tests in human peripheral blood lymphocytes, and was negative in an in vivo micronucleus test in mice after intravenous injection of doses up to 4 mmol/kg.

Impairment of Fertility

Gadoxetate disodium had no effect on fertility and general reproductive performance of male and female rats when given in doses 6.5 times the human dose (based on body surface area).

13.2 Animal Toxicology and/or Pharmacology

A dose-related increase in QTc which was resolved by 30 minutes post dosing was observed in dogs when given a single dose of EOVIST. The increase was noted when given in doses equal to or greater than 0.1 mmol/kg (2.2 times the human dose). Maximum increase in QTcF was equal to or less than 20 ms at doses up to 0.5 mmol/kg (11 times the human dose).

A gait disturbance was observed in 1 of 3 mice when given EOVIST at a dose of approximately 1.1 mmol/kg (3.6 times the human dose); the disturbance occurred at 30 minutes post dosing and resolved at 4 hours post dosing.

Local intolerance reactions, including moderate interstitial hemorrhage, edema, and focal muscle fiber necrosis, were observed after intramuscular administration of EOVIST [see Warning and Precautions (5.5)].

14 CLINICAL STUDIES

The effectiveness of EOVIST was evaluated in patients with suspected or known focal liver lesions in four non-randomized, intrapatient-controlled studies (i.e., Studies 1, 2, 3, and 4). Studies 1 and 2 ("detection" studies) evaluated predominantly the detection of liver lesions and enrolled patients who were scheduled for liver surgery. MRI results were compared to a reference standard that consisted of surgical histopathology and the results from intra-operative ultrasound of the liver. The studies assessed the sensitivity of pre-contrast MRI and EOVIST-contrasted MRI for the detection of liver lesions, when each set of images was compared to the reference.

Studies 3 and 4 ("characterization" studies) evaluated morphological characterization of liver lesions and enrolled patients with known or suspected focal liver lesions, including patients who were not scheduled for liver surgery. MRI results were compared to a reference standard that consisted of surgical histopathology and other prospectively defined criteria. The studies assessed the correctness of liver lesion characterization by pre-contrast MRI and EOVIST-contrasted MRI, when each set of images was compared to the reference. Lesions were characterized as one of the following choices: hepatocellular carcinoma, cholangiocarcinoma, metastasis, focal lymphoma, adenoma, focal nodular hyperplasia, hemangioma, abscess, focal liver fibrosis, regenerative nodule, focal fat, hydatid cyst, liver cyst, "not assessable", normal, no lesion or "other."

In all four studies, patients underwent a baseline, pre-contrast MRI followed by the administration of EOVIST at a dose of 0.025 mmol/kg, with MRI performed immediately (the "dynamic" phase) and at 10 minutes to 20 minutes following EOVIST administration (the "hepatocyte" phase). Patients also underwent computerized tomography with contrast examinations of the liver. Pre-contrast MRI and EOVIST-contrasted MR images were evaluated in a systematic, randomized, paired and unpaired fashion by three radiologists who were blinded to clinical information. CT images were also evaluated by the radiologists in a separate reading session.

Diagnostic efficacy was determined in 621 patients. The average age was 57 years (range 19 to 84 years) and 54% were male. The racial and ethnic representations were 90% White, 4% Black or African American, 3% Hispanic or Latino, 2% Asian, and 1% of other ethnic groups.

The combination of non-contrasted and EOVIST-contrasted MR images had improved sensitivity for the detection and characterization of liver lesions, compared to pre-contrasted MR images (Tables 3 and 4). The improved sensitivity in detection of lesions was predominantly related to the detection of additional lesions among patients with multiple lesions on the pre-contrast MR images. The false positive rates for detection of lesions were similar for non-contrasted MR images and EOVIST-contrasted MR images (32% versus 34%, respectively). Liver lesion detection and characterization results were similar between CT and the combination of pre-contrasted and EOVIST-contrasted MR images.

Table 3: Sensitivity in Liver Lesion Detection
Diagnostic Procedure | Reader | Study 1 Sensitivity (%) n=129 | Study 2 Sensitivity (%) n=126
Pre-contrast MRI | Reader 1 | 76 | 77
Pre-contrast MRI | Reader 2 | 76 | 73
Pre-contrast MRI | Reader 3 | 71 | 72
Combined pre- and EOVIST-contrast MRI | Reader 1 | 81 | 82
Combined pre- and EOVIST-contrast MRI | Reader 2 | 78 | 76
Combined pre- and EOVIST-contrast MRI | Reader 3 | 74 | 78
Difference: combined pre + EOVIST-contrast MRI minus pre MRI (95% confidence interval) | Reader 1 | 5 (1, 9) [Statistically significant improvement] | 5 (1, 9)
Difference: combined pre + EOVIST-contrast MRI minus pre MRI (95% confidence interval) | Reader 2 | 2 (-1, 5) | 3 (-1, 7)
Difference: combined pre + EOVIST-contrast MRI minus pre MRI (95% confidence interval) | Reader 3 | 3 (0, 6) | 6 (0, 10)

Table 4: Proportion of Correctly Characterized Lesions
Diagnostic Procedure | Reader | Study 3 |  | Study 4
Diagnostic Procedure | Reader | n | Proportion correct (%) [Proportion of correctly characterized lesions with respect to the reference] | n | Proportion correct (%)
Pre-contrast MRI | Reader 1 | 182 | 51 | 177 | 60
Pre-contrast MRI | Reader 2 | 182 | 59 | 177 | 64
Pre-contrast MRI | Reader 3 | 182 | 53 | 177 | 48
Combined pre- and EOVIST-contrast MRI | Reader 1 | 182 | 67 | 177 | 61
Combined pre- and EOVIST-contrast MRI | Reader 2 | 182 | 76 | 177 | 76
Combined pre- and EOVIST-contrast MRI | Reader 3 | 182 | 58 | 177 | 67
Difference: combined pre- and EOVIST-contrast MRI minus pre-contrast MRI (95% confidence interval) | Reader 1 |  | 16 (7, 25) [Statistically significant improvement] |  | 1 (-7, 10)
Difference: combined pre- and EOVIST-contrast MRI minus pre-contrast MRI (95% confidence interval) | Reader 2 |  | 17 (9, 25) |  | 11 (5, 18)
Difference: combined pre- and EOVIST-contrast MRI minus pre-contrast MRI (95% confidence interval) | Reader 3 |  | 5 (-2, 12) |  | 19 (11, 27)

16 HOW SUPPLIED/STORAGE AND HANDLING

How Supplied

EOVIST (gadoxetate disodium) injection is supplied at a concentration of 0.25 mmol/mL of gadoxetate disodium as a clear and colorless to pale yellow solution available in the following strengths:

- 2.5 mmol/10 mL (2.5 mmol/mL) in single-dose vials, boxes of 5 (NDC 50419-320-05)
- 3.75 mmol/15 mL (2.5 mmol/mL) in single-dose vials, boxes of 5 (NDC 50419-320-15)

Storage and Handling

Store at 20°C to 25° C (68°F to 77° F); excursions permitted to 15°C to 30° C (59°F to 86°F) [see USP Controlled Room Temperature].

17 PATIENT COUNSELING INFORMATION

Advise the patient to read the FDA-approved patient labeling (Medication Guide).

Nephrogenic Systemic Fibrosis

Inform the patient that EOVIST may increase the risk for NSF among patients with impaired elimination of the drug and that NSF may result in fatal or debilitating fibrosis affecting the skin, muscle, and internal organs.

Instruct the patients to contact their physician if they develop signs or symptoms of NSF following EOVIST administration, such as burning, itching, swelling, scaling, hardening and tightening of the skin; red or dark patches on the skin; stiffness in joints with trouble moving, bending or straightening the arms, hands, legs or feet; pain in the hip bones or ribs; or muscle weakness [see Warnings and Precautions (5.2)].

Gadolinium Retention

Advise patients that gadolinium is retained for months or years in brain, bone, skin, and other organs following EOVIST administration even in patients with normal renal function. The clinical consequences of retention are unknown. Retention depends on multiple factors and is greater following administration of linear GBCAs than following administration of macrocyclic GBCAs [see Warnings and Precautions (5.4)].

Pregnancy

Advise pregnant women of the potential risk of fetal exposure to EOVIST [see Use in Specific Populations (8.1)].

Manufactured for:
Bayer HealthCare Pharmaceuticals Inc.
Whippany, NJ 07981

Manufactured in Germany

© 2008, Bayer HealthCare Pharmaceuticals Inc., All rights reserved.

MEDICATION GUIDE
EOVIST (e-o-vist)
(gadoxetate disodium)
Injection, for intravenous use

What is the most important information I should know about EOVIST?

- GBCAs like EOVIST may cause serious side effects including death, coma, encephalopathy, and seizures when it is given intrathecally (injection given into the spinal canal). It is not known if EOVIST is safe and effective with intrathecal use. EOVIST is not approved for this use.
- EOVIST contains a metal called gadolinium. Small amounts of gadolinium can stay in your body including the brain, bones, skin and other parts of your body for a long time (several months to years).
- It is not known how gadolinium may affect you, but so far, studies have not found harmful effects in patients with normal kidneys.
- Rarely, patients have reported pains, tiredness, and skin, muscle or bone ailments for a long time, but these symptoms have not been directly linked to gadolinium.
- At equivalent doses, the amount of gadolinium that stays in the body is different for different gadolinium medicines. Gadolinium stays in the body more after gadodiamide than after gadoxetate disodium, or gadobenate dimeglumine. Gadolinium stays in the body the least after gadoterate meglumine, gadobutrol, gadoteridol, and gadopiclenol.
- People who get many doses of gadolinium medicines, women who are pregnant and young children may be at increased risk from gadolinium staying in the body.
- Some people with kidney problems who get gadolinium medicines can develop a condition with severe thickening of the skin, muscles and other organs in the body (nephrogenic systemic fibrosis). Your healthcare provider should screen you to see how well your kidneys are working before you receive EOVIST.

What is EOVIST?

- EOVIST is a prescription medicine called a gadolinium-based contrast agent (GBCA). EOVIST, like other GBCAs, is injected into your vein and used with a magnetic resonance imaging (MRI) scanner.
- An MRI exam with a GBCA, including EOVIST, helps your doctor to see problems better than an MRI exam without a GBCA. EOVIST is used to better see the problems in your liver.
- Your doctor has reviewed your medical records and has determined that you would benefit from using a GBCA with your MRI exam.

Do not receive EOVIST if you have had a severe allergic reaction to EOVIST.

Before receiving EOVIST, tell your healthcare provider about all your medical conditions, including if you:

- have had any MRI procedures in the past where you received a GBCA. Your healthcare provider may ask you for more information including the dates of these MRI procedures.
- are pregnant or plan to become pregnant. It is not known if EOVIST can harm your unborn baby. Talk to your healthcare provider about the possible risks to an unborn baby if a GBCA such as EOVIST is received during pregnancy.
- have kidney problems, diabetes, or high blood pressure.
- have had an allergic reaction to dyes (contrast agents) including GBCAs

What are the possible side effects of EOVIST?

- See "What is the most important information I should know about EOVIST?"
- Allergic reactions. EOVIST can cause allergic reactions that can sometimes be serious. Your healthcare provider will monitor you closely for symptoms of an allergic reaction.

The most common side effects of EOVIST include: nausea, headache, feeling hot, dizziness, and back pain.
These are not all the possible side effects of EOVIST.
Call your doctor for medical advice about side effects. You may report side effects to FDA at 1-800-FDA-1088.

General information about the safe and effective use of EOVIST.
Medicines are sometimes prescribed for purposes other than those listed in a Medication Guide. You can ask your healthcare provider for information about EOVIST that is written for health professionals.

What are the ingredients in EOVIST?
Active ingredient: gadoxetate disodium
Inactive ingredients: caloxetate trisodium, trometamol, hydrochloric acid and/or sodium hydroxide (for pH adjustment), and water for injection.
Manufactured for Bayer HealthCare Pharmaceuticals Inc.
Manufactured in Germany
© 2008 Bayer HealthCare Pharmaceuticals Inc. All rights reserved.
For more information, go to www.eovist.com or call 1-888-842-2937.

This Medication Guide has been approved by the U.S. Food and Drug Administration

Revised: 2/2026

Carton 5 x 10 mL

NDC 50419-320-05
5 vials of 10 mL
sterile solution
Eovist® 10 mL
(gadoxetate disodium)
Injection
0.25 mol/L
Rx only
Each mL contains 181.43 gadoxetate disodium and the excipients caloxetate trisodium, trometamol, hydrochloric acid and/or sodium hydroxide (for pH adjustment), and water for injection. Eovist® contains no antimicrobial preservative.
Single-dose container.
Discard unused portion.
Store at 20-25°C (68-77°F); excursions permitted to 15-30°C [See USP Controlled Room Temperature.]
For intravenous administration.
Dosage: See package insert.
Mfd. for:
Bayer HealthCare Pharmaceuticals Inc.
Wayne, NJ 07470
Mfd. in Germany